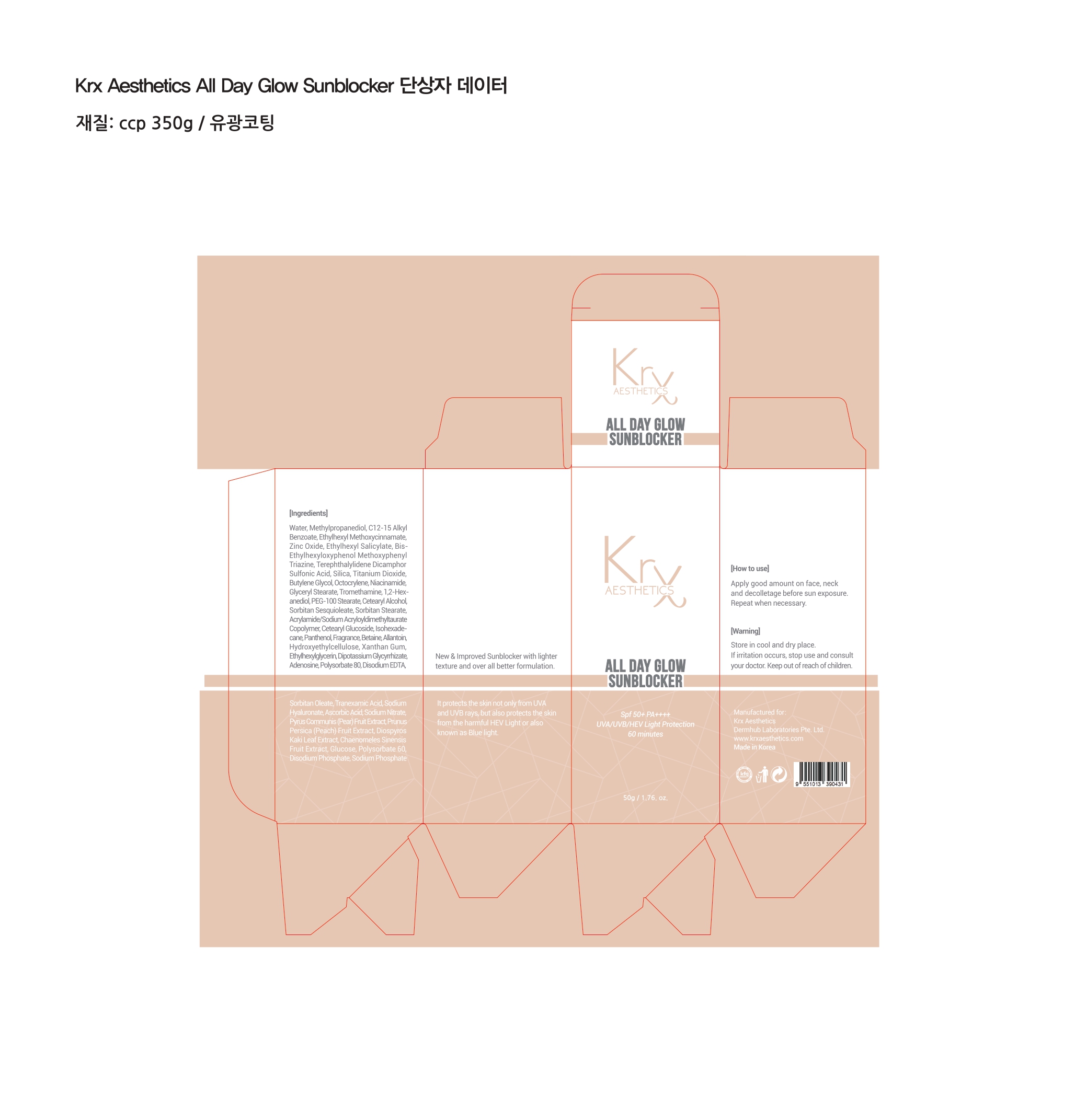 DRUG LABEL: Krx Aesthetics All Day Glow Sunblocker
NDC: 84755-0001 | Form: CREAM
Manufacturer: KRX RESOURCES SDN. BHD.
Category: otc | Type: HUMAN OTC DRUG LABEL
Date: 20251018

ACTIVE INGREDIENTS: OCTOCRYLENE 1 g/50 g; ZINC OXIDE 2.5 g/50 g; TITANIUM DIOXIDE 1 g/50 g
INACTIVE INGREDIENTS: NIACINAMIDE; TROMETHAMINE; ACRYLAMIDE/SODIUM ACRYLOYLDIMETHYLTAURATE COPOLYMER (120000 MPA.S AT 1%); POLYSORBATE 80; S-TRIAZINE; 1,2-HEXANEDIOL; PEG-20 SORBITAN STEARATE; PEG-6 SORBITAN OLEATE; SORBITAN SESQUIOLEATE; SILICA DIMETHYL SILYLATE; BUTYLENE GLYCOL; BETAINE; MAGNESIUM DISODIUM EDTA; PEG-100 STEARATE; PANTHENOL; ALLANTOIN; SODIUM PHOSPHATE P-32, UNSPECIFIED; WATER; ISOHEXADECANE; XANTHAN GUM; POLYSORBATE 60; FRAGRANCE 13576; METHYLPROPANEDIOL; C12-20 ALKYL BENZOATE; CETEARYL GLUCOSIDE; ETHYLHEXYLGLYCERIN; GLYCYRRHIZINATE DIPOTASSIUM; GLYCERYL STEARATE SE

DOSAGE AND ADMINISTRATION

Apply good amount on face, neck and decolletage before sun exposure. Repeat when necessary.

WARNINGS

Store in cool and dry place.
If irritation occurs, stop use and consult your doctor.

Keep out of reach of children.

INACTIVE INGREDIENT

Water, Methylpropanediol, C12-15 Alkyl Benzoate, Ethylhexyl Methoxycinnamate,
Zinc Oxide, Ethylhexyl Salicylate, Bis-Ethylhexyloxyphenol Methoxyphenyl
Triazine, Terephthalylidene Dicamphor Sulfonic Acid, Silica, Titanium Dioxide, Butylene Glycol, Octocrylene, Niacinamide, Glyceryl Stearate, Tromethamine, 1,2-Hex-anediol, PEG- 100 Stearate, Cetearyl Alcohol, Sorbitan Sesquioleate, Sorbitan Stearate, Acrylamide/Sodium Acryloyldimethyltaurate Copolymer, Cetearyl Glucoside, Isohexade-cane, Panthenol, Fragrance, Betaine, Allantoin, Hydroxyethy|cellulose, Xanthan Gum, Ethylhexylglycerin, Dipotassium Glycynhizate, Adenosine, Polysorbate 80, Disodium EDTA, Sorbitan Oleate, Tranexamic Acid, Sodium Hyaluronate, Ascorbic Acid, Sodium Nitrate, Pyrus Communis (Pear) Fruit Extract, Prunus Persica (Peach) Fruit Extract, Diospyros Kaki Leaf Extract, Chaenomeles Sinensis Fruit Extract, Glucose, Polysorbate 60, Disodium Phosphate, Sodium Phosphate

INDICATIONS AND USAGE

ALL DAY GLOW SUNBLOCKER
Spf 50+ PA++++ UVA/UVB/HEV Light Protection 60 minutes

New & Improved Sunblocker with lighter texture and over all better formulation.
It protects the skin not only from UVA and UVB rays, but also protects the skin from the harmful HEV Light or also known as Blue light.

Keep out of reach of children.

PURPOSE

Krx Aesthetics All Day Glow Sunblocker EOE

ALL DAY GLOW
SUNBLOCKER

Active:
Zinc Oxide - 5%
Octocrylene - 2%
Titanium Dioxide -2%

PACKAGE LABEL

New & Improved Sunblocker with lighter texture and over all better formulation.
It protects the skin not only from UVA and UVB rays, but also protects the skin from the harmful HEV Light or also known as Blue light.